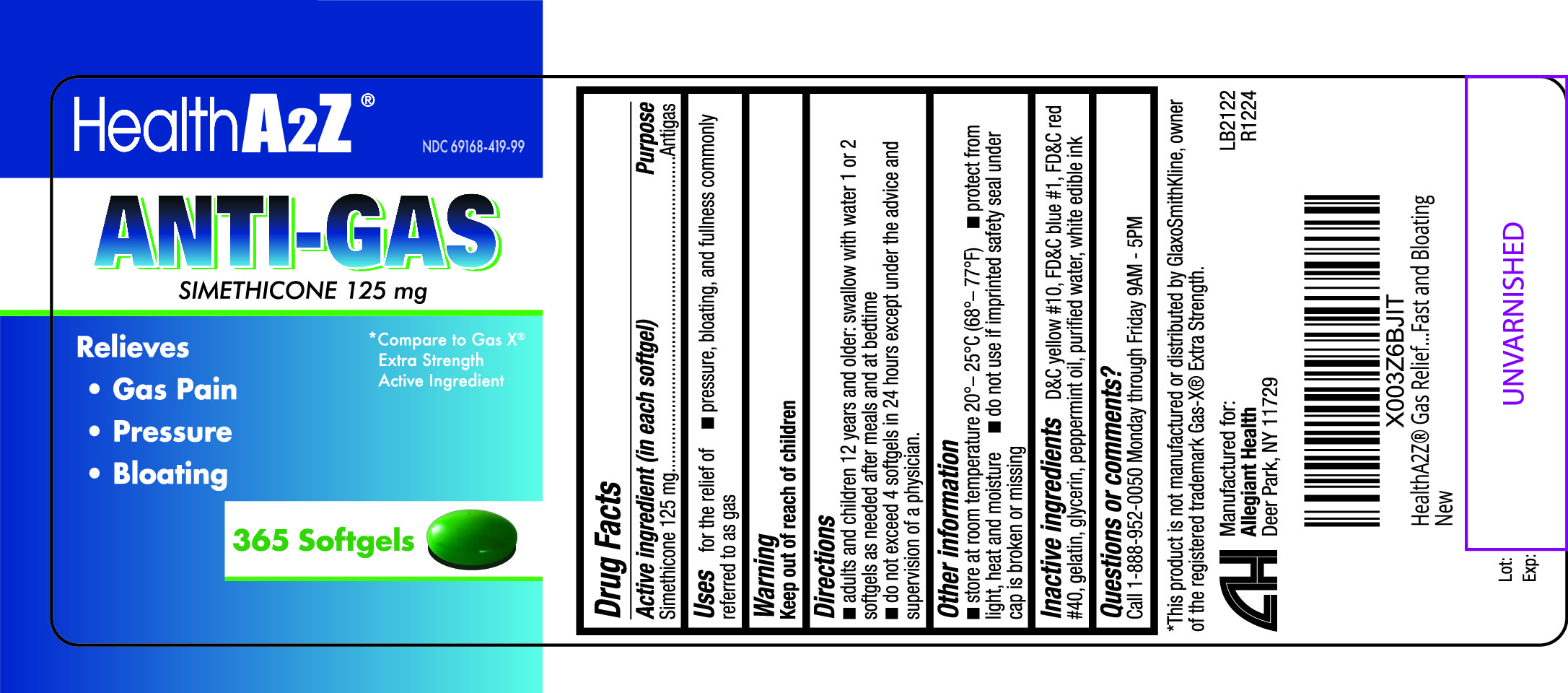 DRUG LABEL: Anti-Gas
NDC: 69168-419 | Form: CAPSULE
Manufacturer: Allegiant Health
Category: otc | Type: HUMAN OTC DRUG LABEL
Date: 20201103

ACTIVE INGREDIENTS: DIMETHICONE 125 mg/1 1
INACTIVE INGREDIENTS: D&C YELLOW NO. 10; FD&C BLUE NO. 1; FD&C RED NO. 40; GELATIN; GLYCERIN; PEPPERMINT OIL; WATER

419- Anti Gas

Active ingredient(s)

Simethicone 125mg

Purpose

Anti gas

Use(s)

for the relief of

- pressure, bloating, and fullness commonly referred to as gas

Directions

- adults and children 12 years and older: swallow with water 1 or 2 softgels as needed after meals and at bedtime
- do not exceed 4 softgels in 24 hours except under the advice and supervision of a physician.

Other information

- Do not use if blister unit is torn or open
- do not use if imprinted safety seal under cap is broken or missing

Storage

- store at room temperature 20o-25oC (68o -77oF)
- protect from light, heat and moisture

Inactive ingredients

D&C yellow #10, FD&C blue #1, FD&C red #40, gelatin, glycerin, peppermint oil, purified water, white edible ink

Questions

Call 1-888-952-0050 Monday through Friday 9AM - 5PM

Principal Display Panel

Gas Relief